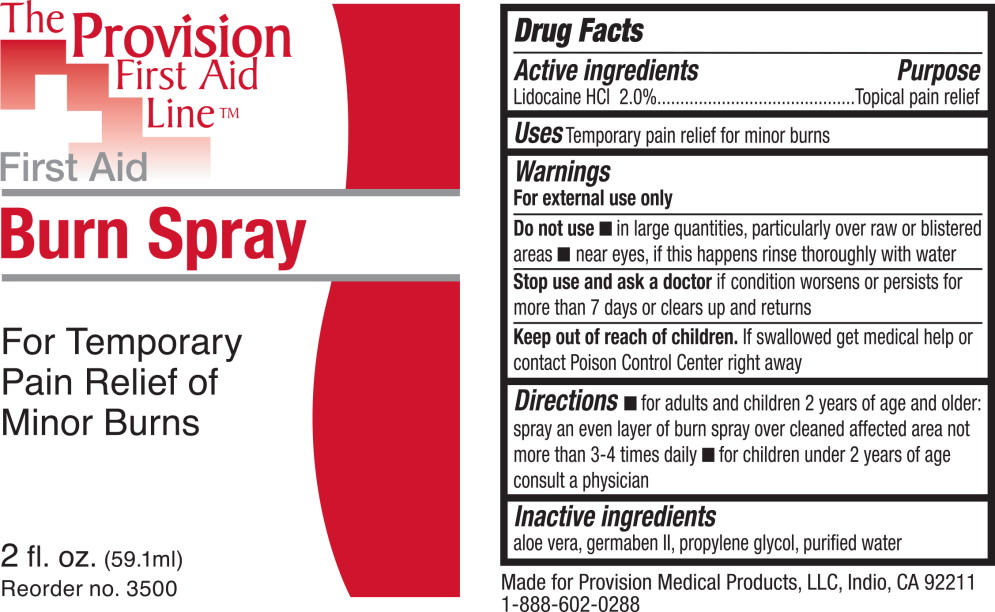 DRUG LABEL: Lidocaine Hydrochloride
NDC: 69103-5100 | Form: LIQUID
Manufacturer: Provision Medical
Category: otc | Type: HUMAN OTC DRUG LABEL
Date: 20131111

ACTIVE INGREDIENTS: Lidocaine Hydrochloride 18 g/1 L
INACTIVE INGREDIENTS: aloe vera leaf; propylene glycol; propylparaben; methylparaben; diazolidinyl urea; water

Drug Facts

Active ingredients

Lidocaine HCl 2.0%

Purpose

Topical pain relief

Uses

Temporary pain relief for minor burns

Warnings

For external use only

Do not use

- in large quantities, particularly over raw or blistered areas
- near eyes, if this happens rinse thoroughly with water

Stop use and ask a doctor if condition worsens or persists for more than 7 days or clears up and returns

Keep out of reach of children. If swallowed get medical help or contact Poison Control Center right away

Directions

- for adults and children 2 years of age and older: spray an even layer of burn spray over cleaned affected area not more than 3-4 times daily
- for children under 2 years of age consult a physician

Inactive ingredients

aloe vera, germaben II, propylene glycol, purified water

Principal Display Panel – 2 fl. oz Bottle Label

The Provision
First Aid
Line™

First Aid
Burn Spray

For Temporary
Pain Relief of
Minor Burns

2 fl. oz. (59.1 ml)

Reorder no. 3500